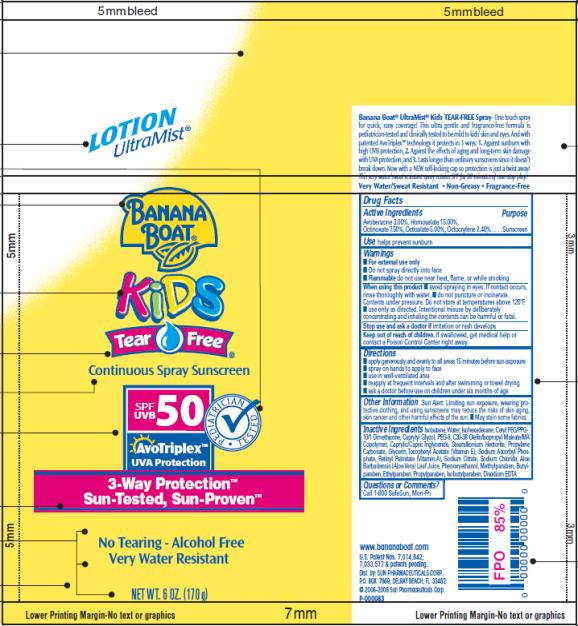 DRUG LABEL: Banana Boat Kids Tear Free Continuous SPF 50
NDC: 17630-2004 | Form: SPRAY
Manufacturer: Accra-Pac, Inc.
Category: otc | Type: HUMAN OTC DRUG LABEL
Date: 20100318

ACTIVE INGREDIENTS: AVOBENZONE 0.03 g/1 g; HOMOSALATE 0.15 g/1 g; OCTINOXATE 0.075 g/1 g; OCTISALATE 0.05 g/1 g; OCTOCRYLENE 0.024 g/1 g
INACTIVE INGREDIENTS: ISOBUTANE; WATER; CAPRYLYL GLYCOL; MEDIUM-CHAIN TRIGLYCERIDES; PROPYLENE CARBONATE; GLYCERIN; .ALPHA.-TOCOPHEROL ACETATE, D-; SODIUM ASCORBYL PHOSPHATE; VITAMIN A PALMITATE; SODIUM CITRATE; ALOE VERA LEAF; PHENOXYETHANOL; METHYLPARABEN; BUTYLPARABEN; ETHYLPARABEN; PROPYLPARABEN; ISOBUTYLPARABEN; EDETATE DISODIUM

Banana Boat Kids Tear Free Continuous Spray SPF 50

Drug Facts

Active Ingredients

Avobenzone 0.03g / 1g

Homosalate 0.15g / 1g

Octinoxate 0.075g / 1g

Octisalate 0.05g / 1g

Octocrylene 0.024g / 1g

Purpose

Sunscreen

Use

helps prevent sunburn

Warnings

- For external use only
- Do not spray directly into face
- Flammable do not use near heat, flame, or while smoking

When using this product

- avoid spraying in eyes. If contact occurs, rinse thoroughly with water.
- do not puncture or incinerate. Contents under pressure. Do not store at temperatures above 120°F.
- use only as directed. Intentional misuse by deliberately concentrating and inhaling the contents can be harmful or fatal.

Stop use and ask a doctor if

irritation or rash develops

Keep out of reach of children.

If swallowed, get medical help or contact a Poison Control Center right away.

Directions

- apply generously and evenly to all areas 15 minutes before sun exposure
- spray on hands to apply to face
- use in well-ventilated area
- reapply at frequent intervals and after swimming or towel drying
- ask a doctor before use on children under six months of age

Other Information

Sun Alert: Limiting sun exposure, wearing protective clothing, and using sunscreens may reduce the risks of skin aging, skin cancer and other harmful effects of the sun.

- May stain some fabrics.

Inactive Ingredients

Isobutane, Water, Isohexadecane, Cetyl PEG/PPG-10/1 Dimethicone, Caprylyl Glycol, PEG-8, C30-38 Olefin/Isopropyl Maleate/MA Copolymer, Caprylic/Capric Triglyceride, Stearalkonium Hectorite, Propylene Carbonate, Glycerin, Tocopheryl Acetate (Vitamin E), Sodium Ascorbyl Phosphate, Retinyl Palmitate (Vitamin A), Sodium Citrate, Sodium Chloride, Aloe Barbadensis (Aloe Vera) Leaf Juice, Phenoxyethanol, Methylparaben, Butylparaben, Ethylparaben, Propylparaben, Isobutylparaben, Disodium EDTA

Questions or Comments?

Call 1-800 SafeSun, Mon-Fri

www.bananaboat.com

Dist. by: SUN PHARMACEUTICALS CORP.
P.O. BOX 7869, DELRAY BEACH, FL 33482

PRINCIPAL DISPLAY PANEL

LOTION
UltraMist®
Banana Boat®
Kids
Tear Free®
Continuous Spray Sunscreen
SPF/UVB 50 Pediatrician Tested
AvoTriplex TM
UVA Protection
3-Way Protection TM
Sun-Tested, Sun-Proven
No Tearing – Alcohol Free
Very Water Resistant
NET WT. 6 OZ. (170 g)